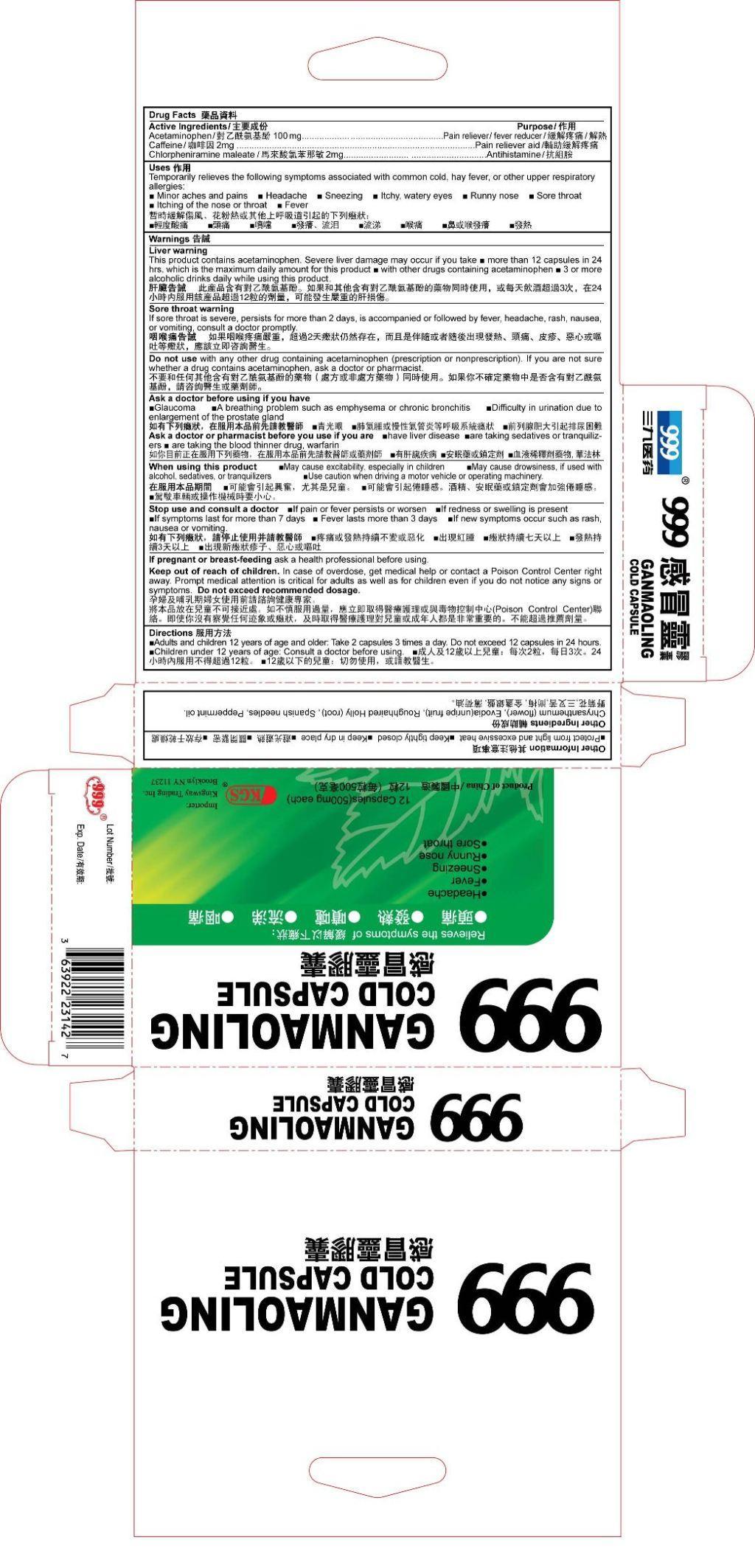 DRUG LABEL: 999 GANMAOLING
NDC: 63922-601 | Form: CAPSULE
Manufacturer: Kingsway
Category: otc | Type: HUMAN OTC DRUG LABEL
Date: 20120703

ACTIVE INGREDIENTS: ACETAMINOPHEN 100 mg/1 1; CAFFEINE 2 mg/1 1; CHLORPHENIRAMINE MALEATE 2 mg/1 1
INACTIVE INGREDIENTS: DENDRANTHEMA INDICUM FLOWER; TETRADIUM RUTICARPUM FRUIT; ILEX PUBESCENS ROOT; BIDENS BIPINNATA WHOLE; PEPPERMINT OIL

Drug Facts

Active Ingredients
Acetaminophen 100 mg
Caffeine 2 mg
Chlorpheniramine Maleate 2 mg

Purpose

Pain reliever/fever reducer

Pain reliever aid

Antihistamine

INDICATIONS AND USAGE

Uses Temporarily relieves the following symptoms associated with the common cold, hay fever or other upper respiratory allergies: • Minor aches an pains • Headache •Sneezing • Muscular aches • Itchy, watery eyes • Runny nose • Sore Throat • Itching of the nose or throat • Fever

Warnings

Liver warningThis product contains acetaminophen, Severe liver damage many occur if you take ■ more than 6 packets in 24 hours, which is the maximum daily amount for this product ■with other drugs containing acetaminophen ■3 or more alcoholic drinks daily while using this product.

Sore throat warning If sore throat is severe, persists for more than 2 days, is accompanied or followed by fever, headache, rash, nausea, or vomiting, consult a doctor promptly.

Ask a doctor before using if you have
• Glaucoma • A breathing problem such as emphysema or chronic bronchitis • Difficulty in urination due to enlargement of the prostate gland

Ask a doctor or pharmacist before use if you are ■have liver disease ■are taking sedatives or tranquilizers ■ are taking the blood thinner drug, warfarin

When using this product ■ May cause excitability, especially in children ■ May cause drowsiness, if used with alcohol, sedatives, or tranquilizers ■ Use caution when driving a motor vehicle or operating machinery.

Stop use and consult a doctor ■ If pain or fever persists or worsen ■ If redness or swelling is present ■ If symptoms last for more than 7 days ■ Fever lasts more than 3 days ■ If new symptoms occur such as rash, nausea or vomiting.

KEEP OUT OF REACH OF CHILDREN

If pregnant or breast-feeding ask a health professional before using.
Keep out of reach of children. In case of overdose, get medical help or contact a Poison Control Center right away. Prompt medical attention is critical for adults as well as for children even if you do not notice any signs of symptoms. Do not exceed recommended

DOSAGE AND ADMINISTRATION

Directions■ Adults and children 12 years of age and older: Take 2 capsules 3 times a day. Do not exceed 12 capsules in 24 hours.
■ Children under 12 years of age: Consult a doctor before using.

Other Information
■ Protect form light and excessive heat ■ Keep tightly closed ■ Keep in dry place

INACTIVE INGREDIENT

Other Ingredients
Chrysanthemum (flower), Evodia (unripe fruit), Roughhaired Holly (root), Spanish needles, Peppermint oil.